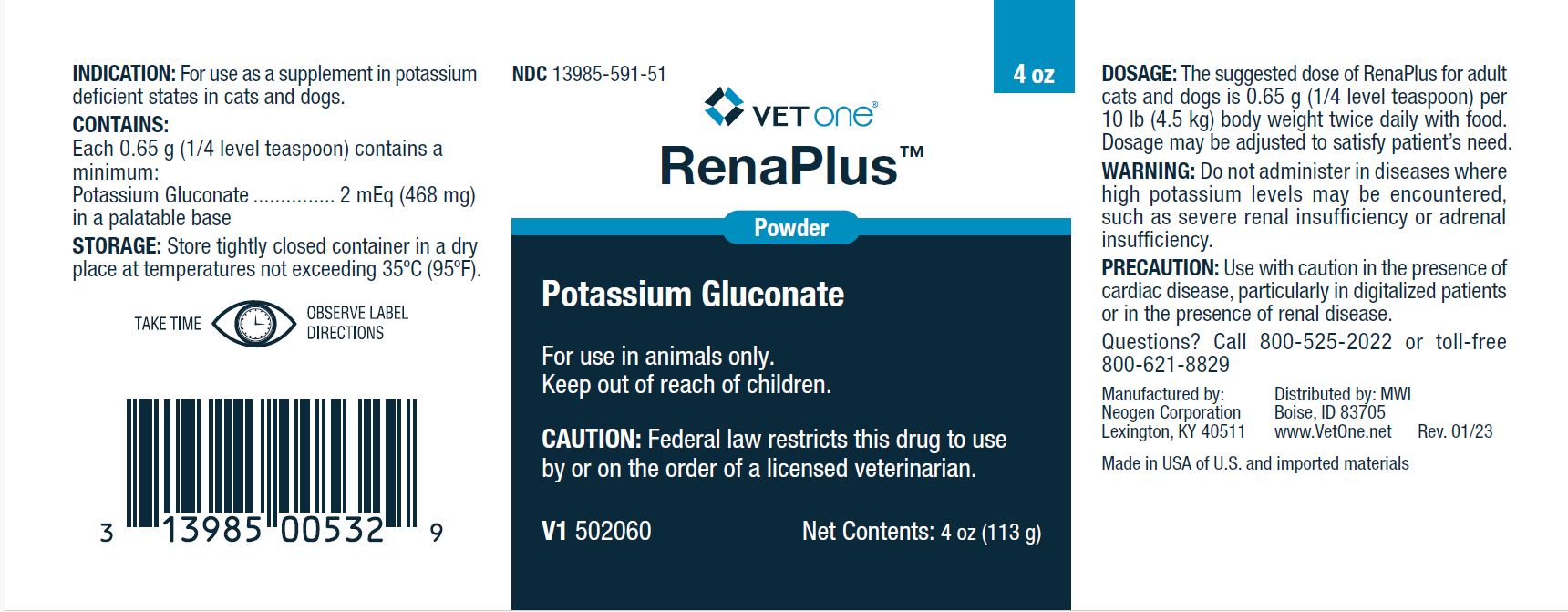 DRUG LABEL: RenaPlus
NDC: 13985-591 | Form: Powder
Manufacturer: MWI/VetOne
Category: animal | Type: PRESCRIPTION ANIMAL DRUG LABEL
Date: 20240510

ACTIVE INGREDIENTS: POTASSIUM GLUCONATE 468 mg/0.65 g
INACTIVE INGREDIENTS: SILICON DIOXIDE

DESCRIPTION

VETone®

RenaPlus Powder™

Potassium Gluconate

For use in animals only.

CONTAINS:

Each 0.65 g (1/4 level teaspoon) contains a minimum:

Potassium gluconate..............................2 mEq (468 mg)

in a palatable base.

DOSAGE:

The suggested dose of RenaPlus for adult cats and dogs is 0.65 g (1/4 level teaspoon) per 10 lb (4.5 kg) body weight twice daily with food. Dosage may be adjusted to satisfy patient's need.

PRECAUTION:

Use with caution in the presence of cardiac disease, particularly in digitalized patients or in the presence of renal disease.

Questions? Call 800-525-2022 or toll-free 800-621-8829

WARNING:

Do not administer in diseases where high potassium levels may be encountered, such as severe renal insufficiency or adrenal insufficiency.

INDICATION:

For use as a supplement in potassium deficient states in cats and dogs.

STORAGE:

Store tightly closed container in a dry place at a temperature not exceeding 35°C (95°F).

Manufactured by:

Neogen Corporation

Lexington, KY 40511

Distributed by: MWI

Boise, ID 83705

www.VetOne.net Rev. 01/23

Made in USA of U.S. and imported materials

PRINCIPAL DISPLAY PANEL - 4 oz Bottle

NDC 13985-591-51

VETone®

RenaPlus Powder™

Potassium Gluconate

For use in animals only.

Keep out of reach of children.

CAUTION: Federal law restricts this drug to use by or on the order of a licensed veterinarian.

V1 502060

Net Contents: 4 oz (113 g)